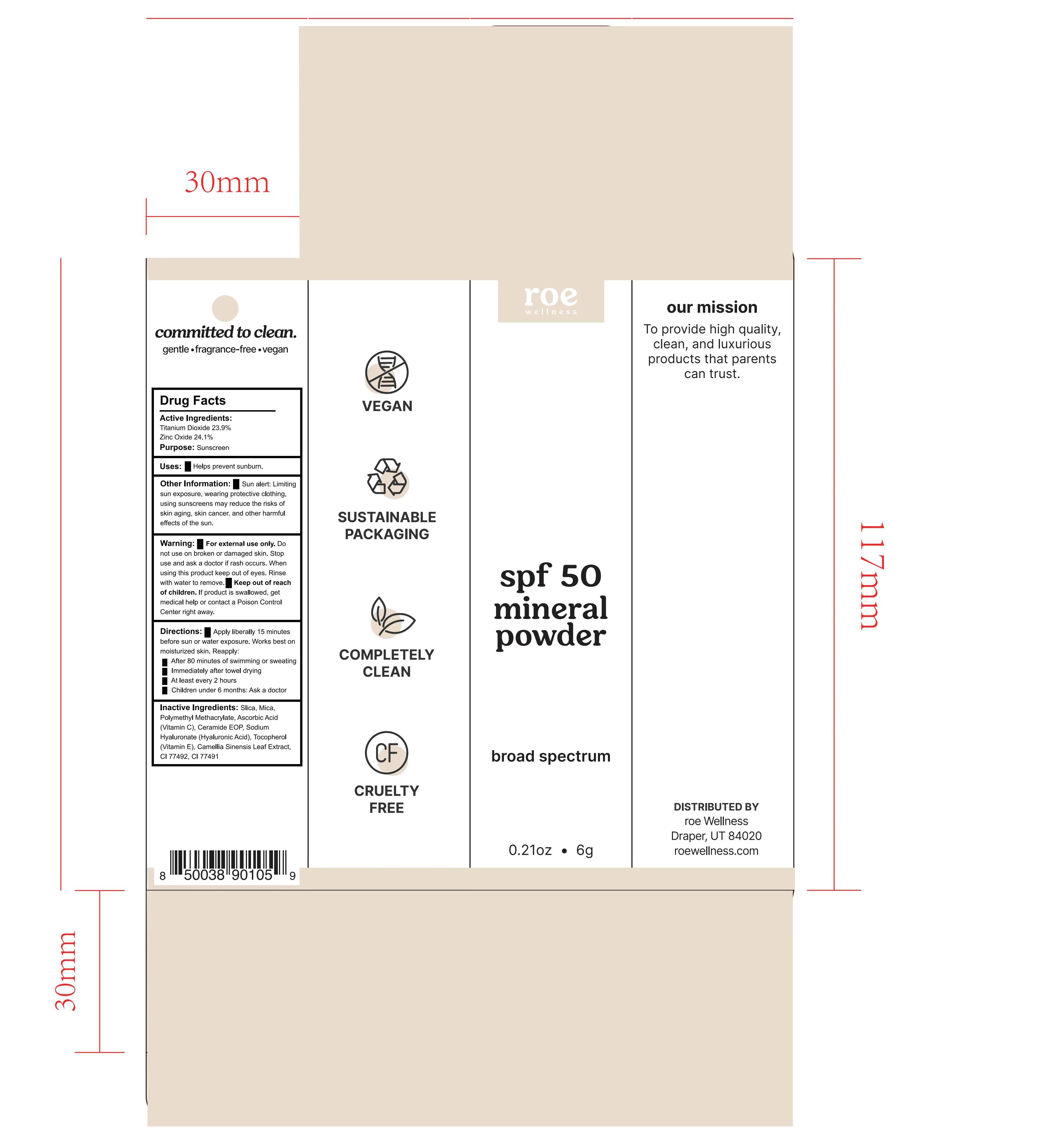 DRUG LABEL: ROE wellness spf 50 mineral powder
NDC: 82723-003 | Form: POWDER
Manufacturer: Aopline Health Industry Technology (Guangzhou) Co., Ltd.
Category: otc | Type: HUMAN OTC DRUG LABEL
Date: 20250108

ACTIVE INGREDIENTS: TITANIUM DIOXIDE 23.9 g/100 g; ZINC OXIDE 24.1 g/100 g
INACTIVE INGREDIENTS: CERAMIDE NP; HYALURONATE SODIUM; ETHYL ACRYLATE AND METHYL METHACRYLATE COPOLYMER DISPERSION (2:1; 600000 MW 30% AQUEOUS); .ALPHA.-TOCOPHEROL CALCIUM SUCCINATE, DL-

82723-003
ROE wellness spf 50 mineral powder

Active Ingredients

Titanium Dioxide 23.9%
Zinc Oxide 24.1%

Purpose

Sunscreen

Uses

Uses: Helps prevent sunburn.

Warnings

For external use only .
Do not use on broken or damaged skin .
Stop use and ask a doctor if rash occurs
When using this product keep out of eyes . Rinse with water to remove .
Keep out of reach of children . If product is swallowed , get medical help or contact a Poison Control Center right away .

Directions

Directions : Apply liberally 15 minutes before sun or water exposure. Works best on moisturized skin.
Reapply:
After 80 minutes of swimming or sweating.
Immediately after towel drying.
At least every 2 hours.
Children under 6 months: Ask a doctor.

Other Information

Other Information : Sun alert : Limiting sun exposure , wearing protective clothing , using sunscreens may reduce the risks of skin aging , skin cancer , and other harmful effects of the sun

Inactive Ingredients

Inactive Ingredients: Slica , Mica, Polymethyl Methacrylate, Ascorbic Acid (Vitamin C), Ceramide EOP, Sodium Hyaluronate (Hyaluronic Acid), Tocopherol Vitamin E), Camellia Sinensis Leaf Extract, CI 77492, CI 77491

Keep out of reach of children . If product is swallowed , get medical help or contact a Poison Control Center right away .

Stop use

Stop use and ask a doctor if rash occurs
When using this product keep out of eyes . Rinse with water to remove .

When using this product keep out of eyes . Rinse with water to remove .
Keep out of reach of children . If product is swallowed , get medical help or contact a Poison Control Center right away .

Do not use on broken or damaged skin .
Stop use and ask a doctor if rash occurs

Package Label

82723-003-01